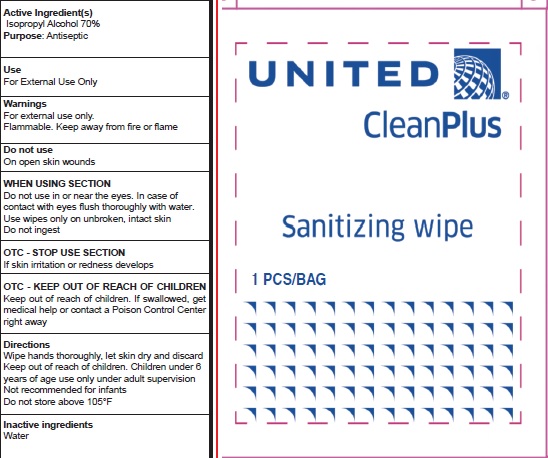 DRUG LABEL: UNITED CleanPlus Sanitizing Wipe
NDC: 78724-010 | Form: SWAB
Manufacturer: Jiebao Daily Chemical (Xiangxi)Co.,Ltd
Category: otc | Type: HUMAN OTC DRUG LABEL
Date: 20200828

ACTIVE INGREDIENTS: ISOPROPYL ALCOHOL 70 g/100 g
INACTIVE INGREDIENTS: water

Wipes

Active Ingredient

ISOPROPYL ALCOHOL ........... 70%

Purpose

Antiseptic

USE

- Help reduce bacteria on the hands

Warning

- Flammable, keep away from fire or flame.
- For external use only.

Do not use On open skin wounds

- When using this product, Do not use in or near the eyes. In case of contact with eyes flush thoroughly with water. USE wipes only on unbroken, instact skin.

Do not ingest

- Stop use and ask a doctor if irritatio or redness develops.

Other information:

- Do not store above 105℉

KEEP OUT OF REACH OF CHILDREN

●If swallowed, get medical help or contact a Poison Contrl Center right away.

Directions

- Wipe hands thoroughly. Let skin dry and discard
- Keep out of reach of children under 6 years of age use only under adult supervision.
- Not recommended for infants

Inactive ingredients

Water